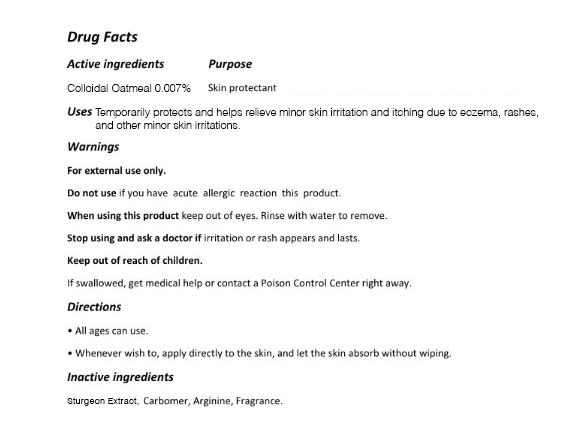 DRUG LABEL: The Zoeun Skin Total Care Cream
NDC: 83636-122 | Form: CREAM
Manufacturer: Sturgeonbio Co.,Ltd.
Category: otc | Type: HUMAN OTC DRUG LABEL
Date: 20251001

ACTIVE INGREDIENTS: OATMEAL 0.007 g/100 mL
INACTIVE INGREDIENTS: CARBOMER HOMOPOLYMER, UNSPECIFIED TYPE; STURGEON, UNSPECIFIED; FRAGRANCE FLORAL ORC0902236; ARGININE

122 THE ZOEUN SKIN TOTAL CARE CREAM

Active Ingredients

Colloidal Oatmeal 0.007%

Purpose

Skin Protectant

Uses

Temporarily protects and helps relieve minor skin irritation and itching due to eczema, rashes, insect bites, and other minor skin irritations.

Warnings

For external use only.

Warnings

Do not use if you have acute allergic reaction this product.

Warnings

- Keep out of reach of children.
- If swallowed, get medical help or contact a Poison Control Center right away.

Warnings

Stop using and ask a doctor if irritation or rash appears and lasts.

Warnings

When using this product keep out of eyes. Rinse with water to remove.

Directions

- All ages can use.
- Whenever wish to, apply directly to the skin, and let the skin absorb without wiping.

Inactive ingredients

Sturgeon Extract, Carbomer, Arginine, Fragrance.